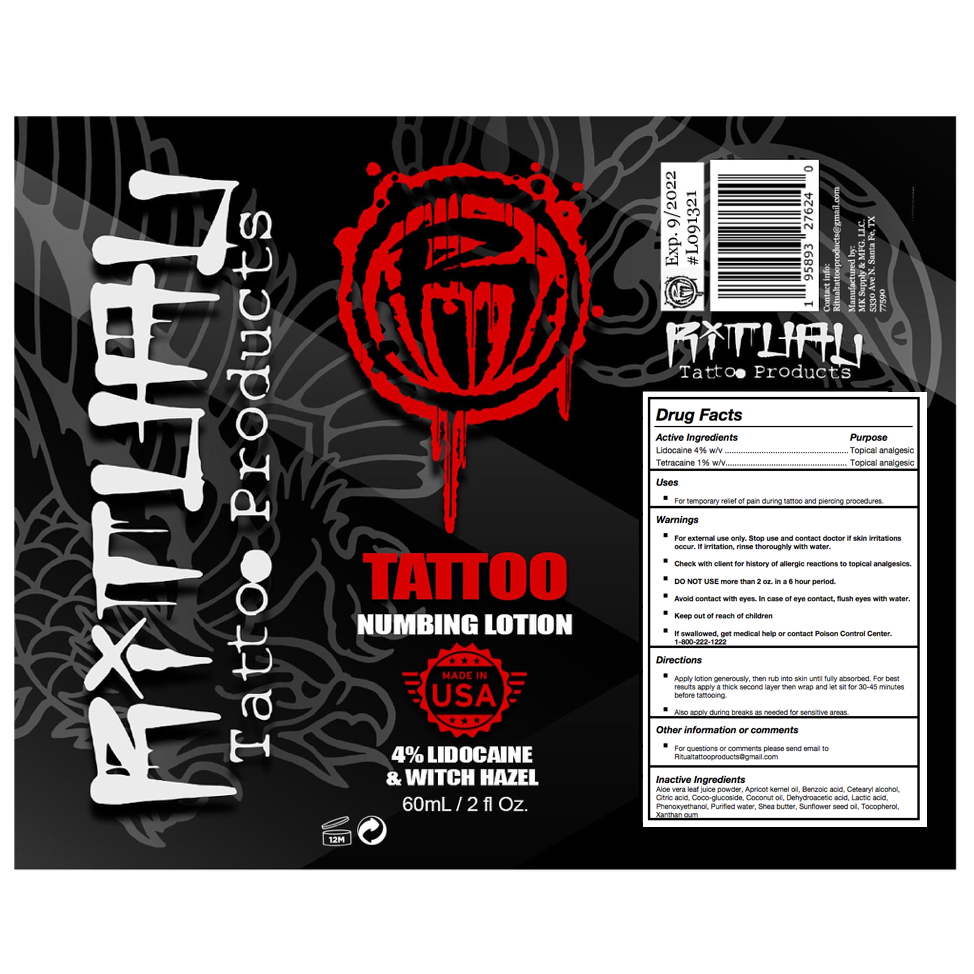 DRUG LABEL: Ritual Tattoo
NDC: 82171-001 | Form: LOTION
Manufacturer: MK Laboratory
Category: otc | Type: HUMAN OTC DRUG LABEL
Date: 20220201

ACTIVE INGREDIENTS: TETRACAINE 1 g/100 mL; LIDOCAINE 4 g/100 mL
INACTIVE INGREDIENTS: ALOE VERA LEAF; CETOSTEARYL ALCOHOL; COCONUT OIL; SUNFLOWER OIL; TOCOPHEROL; LACTIC ACID; APRICOT KERNEL OIL; WATER; BENZOIC ACID; CITRIC ACID MONOHYDRATE; COCO GLUCOSIDE; DEHYDROACETIC ACID; PHENOXYETHANOL; SHEA BUTTER; XANTHAN GUM

Ritual Tattoo Numbing Lotion

Active Ingredients

Lidocaine 4% w/v. Purpose: Topical analgesic

Tetracaine 1% w/v. Purpose: Topical analgesic

Purpose

Lidocaine 4% w/v. Purpose: Topical analgesic

Tetracaine 1% w/v. Purpose: Topical analgesic

Uses

For temporary relief of pain during tattoo and piercing procedures.

Warnings

- For external use only.
- Check with client for history of allergic reactions to topical analgesics.

DO NOT USE more than 2 oz. in a 6 hour period.

WHEN USING

- Avoid contact with eyes. In case of eye contact, flush eyes with water.
- If swallowed, get medical help or contact Poison Control Center. 1-800-222-1222

Stop use and contact doctor if skin irritations occur. If irritation, rinse thoroughly with water.

Keep out of reach of children

Directions

- Apply lotion generously, then rub into skin until fully absorbed. For best results apply a thick second layer then wrap and let sit for 30-45 minutes before tattooing.
- Also apply during breaks as needed for sensitive areas.

Other Information or Comments

For questions or comments please send email to Ritualtattooproducts@gmail.com

Inactive Ingredients

Aloe vera leaf juice powder, Apricot kernel oil, Benzoic acid, Cetearyl alcohol, Citric acid, Coco-glucoside, Coconut oil, Dehydroacetic acid, Lactic acid, Phenoxyethanol, Purified water, Shea butter, Sunflower seed oil, Tocopherol, Xanthan gum

Principal Display Panel

60 mL NDC: 82171-001-60